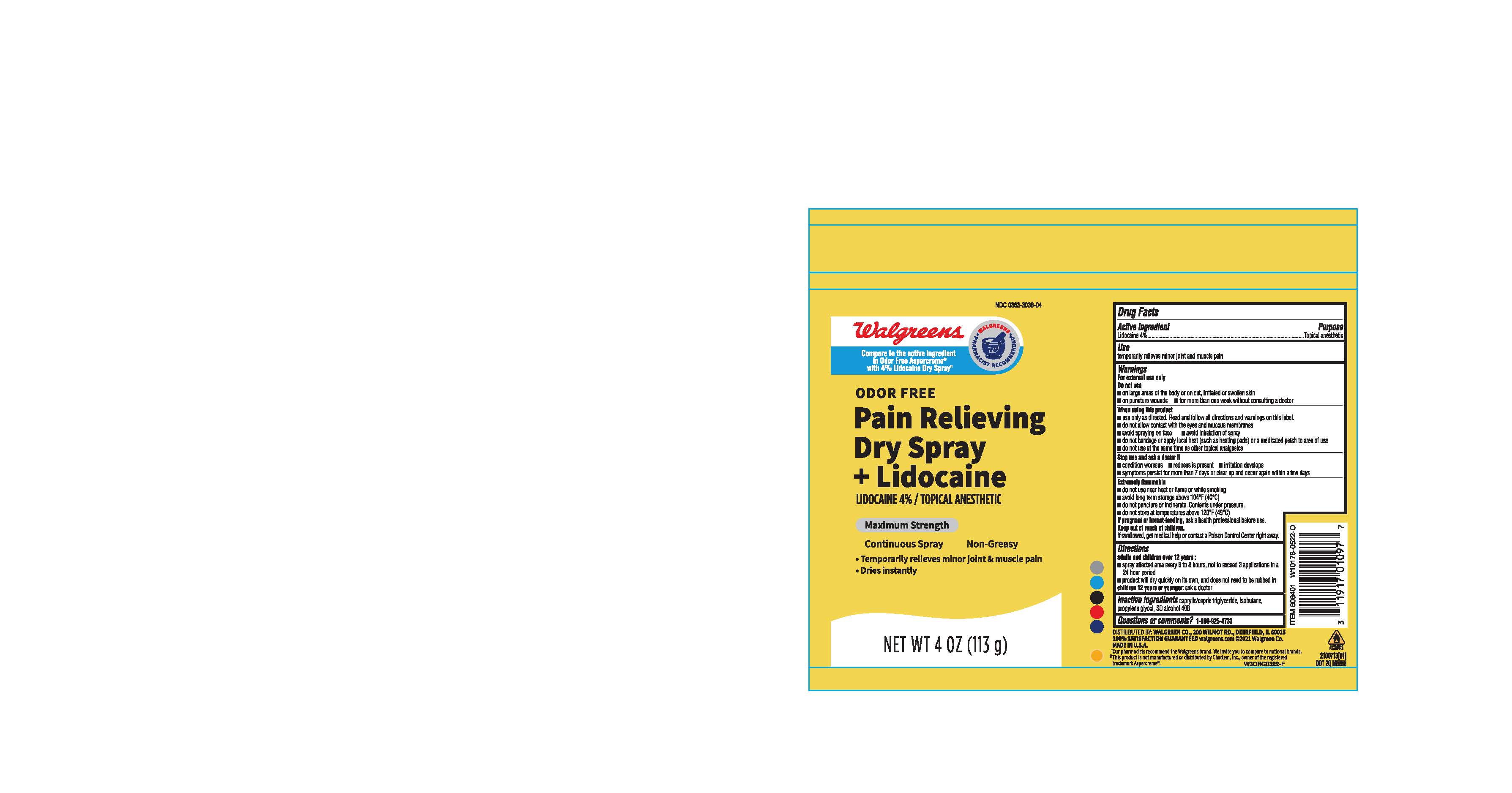 DRUG LABEL: Walgreens pain relieving
NDC: 0363-3038 | Form: AEROSOL, SPRAY
Manufacturer: Walgreens
Category: otc | Type: HUMAN OTC DRUG LABEL
Date: 20231031

ACTIVE INGREDIENTS: LIDOCAINE 4 g/100 g
INACTIVE INGREDIENTS: ISOBUTANE; MEDIUM-CHAIN TRIGLYCERIDES; PROPYLENE GLYCOL; DEHYDRATED ALCOHOL

Pain relieving lidocaine 4% dry spray

ACTIVE INGREDIENT

Lidocaine 4%

PURPOSE

Topical anesthetic

INDICATIONS AND USAGE

temporarily relieves minor joint and muscle pain

WARNINGS

For External use only

Do not use

on large areas of the body or on cut, irritated or swollen skin

on puncture wounds

for more than one week without consulting a doctor

Extremely Flammable

do not use near heat or flame or while smoking

avoid long term storage above 104° F (40°C)

do not puncture or incinerate. Contents under pressure.

do not store at temperatures above 120F (49°C)

When using this product

use only as directed. Read and follow all directions and warnings on this label.

do not allow contact with the eyes and mucous membranes

avoid spraying on face

avoid inhalation of spray

do not bandage or apply local heat (such as heating pads) or a medicated patch to area of use

do not use at the same time as other topical analgesics

PREGNANCY OR BREAST FEEDING

If pregnant or breast-feeding, ask a health professional before use

Keep out of reach of children

if swallowed, get medical help or contact Poison Control Center Right Away

Stop use and ask a doctor if

condition worsens

redness is present

irritation develops

symptoms persist for more than 7 days or clear up and occur again within few days

DOSAGE AND ADMINISTRATION

adults and children over 12 years :

spray affected area every 6 to 8 hours, not to exceed 3 applications in a 24 hour period

product wil dry quickly on its own, and does not need to be rubbed in

children 12 years or younger: ask a doctor

INACTIVE INGREDIENT

caprylic/capric triglyceride, isobutane, propylene glycol, SD alcohol 40 B (30%)

QUESTIONS

1-800-925-4733